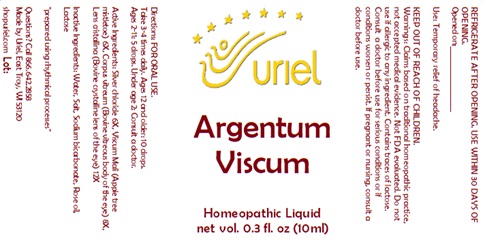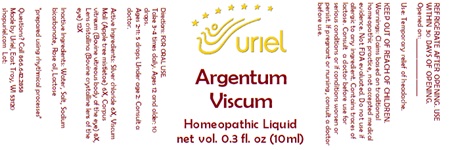 DRUG LABEL: Argentum Viscum
NDC: 48951-1313 | Form: LIQUID
Manufacturer: Uriel Pharmacy Inc.
Category: homeopathic | Type: HUMAN OTC DRUG LABEL
Date: 20240118

ACTIVE INGREDIENTS: SILVER CHLORIDE 6 [hp_X]/1 mL; VISCUM ALBUM FRUITING TOP 6 [hp_X]/1 mL; BOS TAURUS EYE 8 [hp_X]/1 mL
INACTIVE INGREDIENTS: SODIUM CHLORIDE; WATER; SODIUM BICARBONATE; ROSE OIL; LACTOSE, UNSPECIFIED FORM

Argentum Viscum

INDICATIONS AND USAGE

Directions: FOR ORAL USE.

DOSAGE AND ADMINISTRATION

Take 3-4 times daily. Ages 12 and older: 10 drops. Ages 2-11: 5 drops. Under age 2: Consult a doctor.

ACTIVE INGREDIENT

Active Ingredients: Silver chloride 6X, Viscum Mali (Apple tree mistletoe) 6X, Corpus vitreum (Bovine vitreous body of the eye) 8X, Lens cristallina (Bovine crystalline lens of the eye) 12X

INACTIVE INGREDIENT

Inactive Ingredients: Water, Sodium chloride, Boric acid, Sodium bicarbonate, Rose oil, Lactose

"prepared using rhythmical processes"

PURPOSE

Use: Temporary relief of headache.

KEEP OUT OF REACH OF CHILDREN.

WARNINGS

Warnings: Claims based on traditional homeopathic practice, not accepted medical evidence. Not FDA evaluated. Do not use if allergic to any ingredient. Contains traces of lactose. Consult a doctor before use for serious conditions or if conditions worsen or persist. If pregnant or nursing, consult a doctor before use. Do not use if safety seal is broken or missing.

REFRIGERATE AFTER OPENING. USE WITHIN 30 DAYS OF OPENING.
Opened on:_________________

Questions? Call 866.642.2858
Made by Uriel, East Troy, WI 53120
shopuriel.com